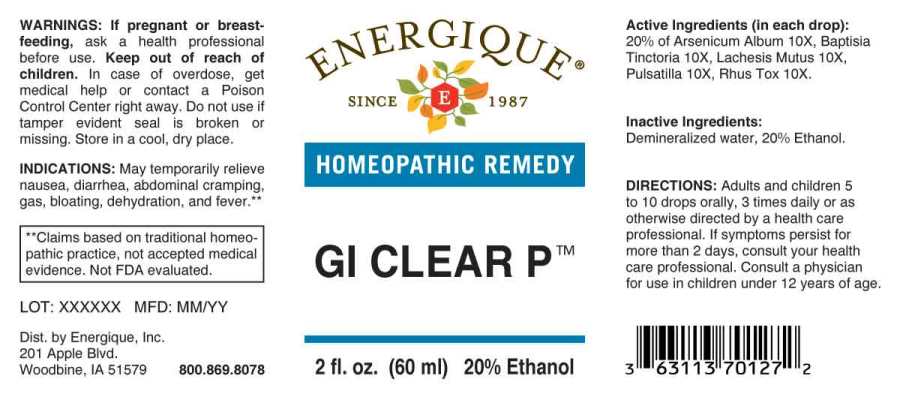 DRUG LABEL: GI Clear P
NDC: 44911-0611 | Form: LIQUID
Manufacturer: Energique, Inc.
Category: homeopathic | Type: HUMAN OTC DRUG LABEL
Date: 20250516

ACTIVE INGREDIENTS: ARSENIC TRIOXIDE 10 [hp_X]/1 mL; BAPTISIA TINCTORIA ROOT 10 [hp_X]/1 mL; LACHESIS MUTA VENOM 10 [hp_X]/1 mL; PULSATILLA PRATENSIS WHOLE 10 [hp_X]/1 mL; TOXICODENDRON PUBESCENS LEAF 10 [hp_X]/1 mL
INACTIVE INGREDIENTS: WATER; ALCOHOL

DRUG FACTS:

ACTIVE INGREDIENTS:

(in each drop): 20% of Arsenicum Album 10X, Baptisia Tinctoria 10X, Lachesis Mutus 10X, Pulsatilla (Pratensis) 10X, Rhus Tox 10X.

INDICATIONS:

May temporarily relieve nausea, diarrhea, abdominal cramping, gas, bloatin, dehydration, and fever.**

**Claims based on traditional homeopathic practice, not accepted medical evidence. Not FDA evaluated.

WARNINGS:

If pregnant or breast-feeding, ask a health professional before use.

Keep out of reach of children. In case of overdose, get medical help or contact a Poison Control Center right away.

Do not use if tamper evident seal is broken or missing. Store in a cool, dry place.

Keep out of reach of children. In case of overdose, get medical help or contact a Poison Control Center right away.

DIRECTIONS:

Adults and children 5 to 10 drops orally, 3 times daily or as otherwise directed by a health care professional. If symptoms persist for more than 2 days, consult your health care professional. Consult a physician for use in children under 12 years of age.

INDICATIONS:

May temporarily relieve nausea, diarrhea, abdominal cramping, gas, bloatin, dehydration, and fever.**

**Claims based on traditional homeopathic practice, not accepted medical evidence. Not FDA evaluated.

INACTIVE INGREDIENTS:

Demineralized water, 20% Ethanol.

QUESTIONS:

Dist. by Energique, Inc.

201 Apple Blvd

Woodbine, IA 51579 800.869.8078

PACKAGE LABEL DISPLAY:

ENERGIQUE

SINCE 1987

HOMEOPATHIC REMEDY

GI CLEAR P

2 fl. oz. (60 ml)